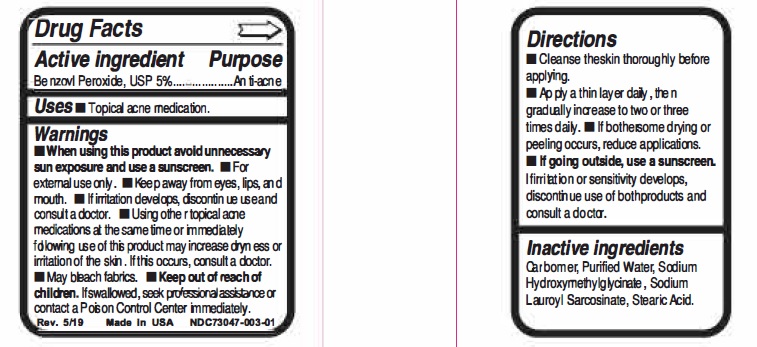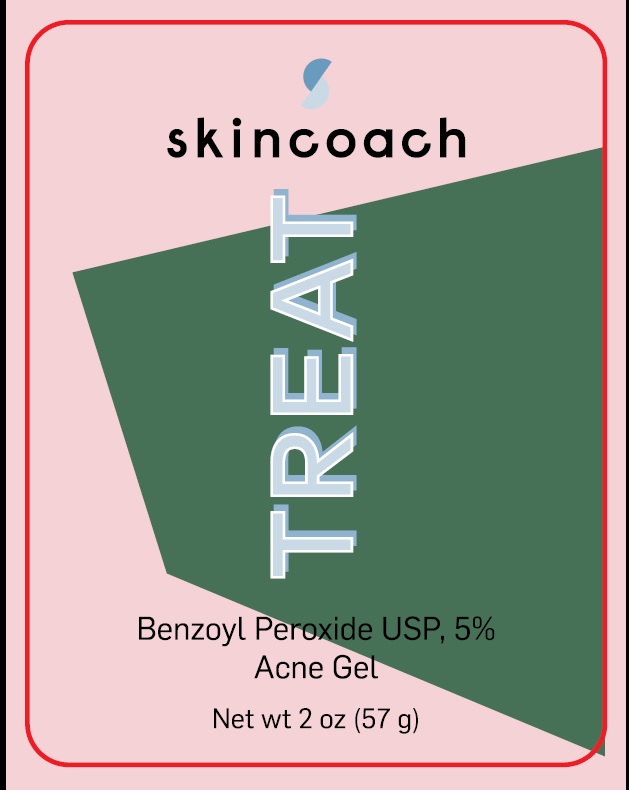 DRUG LABEL: Skincoach TREAT
NDC: 73047-003 | Form: GEL
Manufacturer: SKIN COACH SL.
Category: otc | Type: HUMAN OTC DRUG LABEL
Date: 20190521

ACTIVE INGREDIENTS: BENZOYL PEROXIDE 5 g/100 g
INACTIVE INGREDIENTS: CARBOXYPOLYMETHYLENE; WATER; SODIUM HYDROXYMETHYLGLYCINATE; SODIUM LAUROYL SARCOSINATE; STEARIC ACID

Active ingredient Purpose

Benzoyl Peroxide USP 5%------------ Anti-acne

Uses

Topical acne medication.

Warnings

When using this product avoid unnecessary sun exposure and use a sunscreen. ■ For external use only ■ Keep away from eyes, lips, and mouth ■ If irritation develops discontinue use and consult a doctor ■ Using other topical acne medications at the same time or immediately,
following use of this product may increase dryness or irritation of the skin. If this occurs consult a doctor. ■May bleach fabrics.

KEEP OUT OF REACH OF CHILDREN

Keep out of the reach of childen. If swallowed, seek professional assistance or contact a Poison Control Center immediately.

Directions

■ Cleanse the skin thoroughly belore applying. ■ Apply a thin layer daily,then gradually increase to two or three times daily. ■ If bothersome drying or peeling occurs, reduce applications. ■ If going outside, use a sunscreen. If initation or sensitivity develops, discontinue use of both products and consult a doctor.

Inactive ingredients

Carbomer, Purified Water, Sodium hydroxymethylglycinate, Sodium Lauroyl sarcosinate, Stearic Acid.